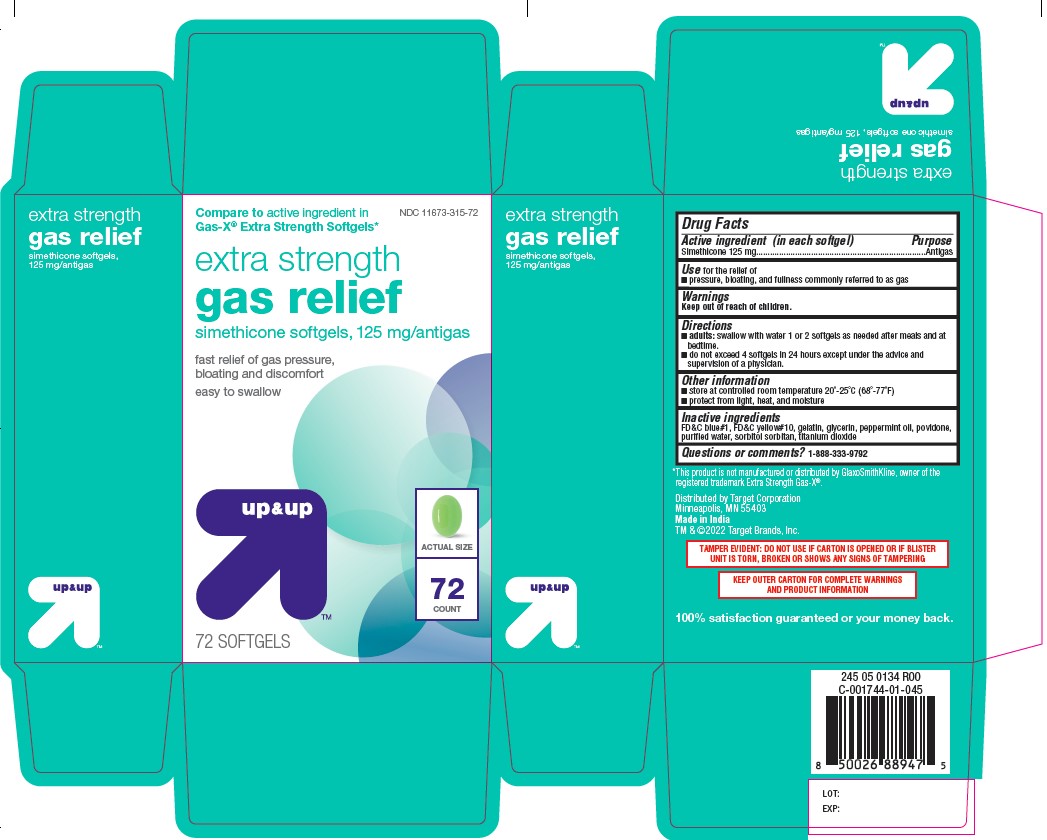 DRUG LABEL: extra strength gas relief simethicone 125 mg
NDC: 11673-415 | Form: CAPSULE, LIQUID FILLED
Manufacturer: Target Corporation
Category: otc | Type: HUMAN OTC DRUG LABEL
Date: 20241230

ACTIVE INGREDIENTS: DIMETHICONE 125 mg/1 1
INACTIVE INGREDIENTS: PEPPERMINT OIL; GELATIN; GLYCERIN; SORBITOL SOLUTION 70%; POVIDONE; FD&C BLUE NO. 1; D&C YELLOW NO. 10; TITANIUM DIOXIDE; WATER

extra strength gas relief simethicone 125 mg

Active ingredient (in each softgel)

Simethicone 125 mg

Purpose

Antigas

Use

for the relief of

- pressure, bloating, and fullness commonly referred to as gas

Directions

adults:

- swallow with water 1 or 2 softgels as needed after meals and at bedtime.
- do not exceed 4 softgels in 24 hours except under the advice and supervision of a physician.

Other information

- store at controlled room temperature 20°-25°C (68°-77°F)
- protect from light, heat, and moisture

Inactive ingredients

FD&C blue#1, FD&C yellow#10, gelatin, glycerin, peppermint oil, povidone,
purified water, sorbitol sorbitan, titanium dioxide

Questions or comments?

1-888-333-9792

Carton

This product is not manufactured or distributed by GlaxoSmithKline, owner of the
registered trademark Extra Strength Gas-X®.

Distributed by Target Corporation
Minneapolis, MN 55403
Made in India
TM & ©2022 Target Brands, Inc.

TAMPER EVIDENT: DO NOT USE IF CARTON IS OPENED OR IF BLISTER
UNIT IS TORN, BROKEN OR SHOWS ANY SIGNS OF TAMPERING
KEEP OUTER CARTON FOR COMPLETE WARNINGS
AND PRODUCT INFORMATION

Carton